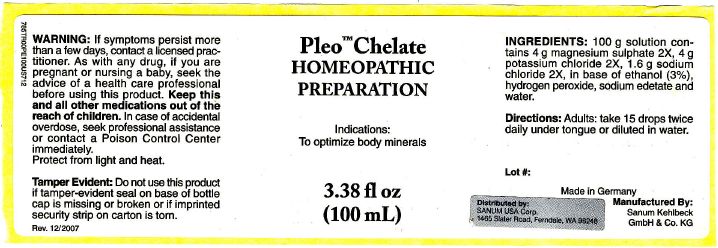 DRUG LABEL: Pleo Chelate
NDC: 60681-6100 | Form: SOLUTION/ DROPS
Manufacturer: Sanum Kehlbeck GmbH & Co. KG
Category: homeopathic | Type: HUMAN OTC DRUG LABEL
Date: 20091125

ACTIVE INGREDIENTS: magnesium sulfate 2 [hp_X]/100 mL; potassium chloride 2 [hp_X]/100 mL; sodium chloride 2 [hp_X]/100 mL
INACTIVE INGREDIENTS: water; edetate sodium; hydrogen peroxide; alcohol

Pleo™ Chelate
DROPS 2X

Homeopathic PREPARATION

3.38 fl oz
(100 mL)

Indications

To optimize body minerals

INGREDIENTS

100g solution contains 4g magnesium sulphate 2X, 4g potassium chloride 2X, 1.6g sodium chloride 2X, sodium edetate, hydrogen peroxide, water, alcohol 3% by volume.

Tamper Evident

Do not use this product if tamper-evident seal on base of bottle cap is missing or broken or if imprinted security strip on carton is torn.

DOSAGE

Adults: take 15 drops twice daily under tongue or diluted in water, unless otherwise recommended by your health professional.

WARNING

If symptoms persist more than a few days, contact a licensed practitioner. As with any other drug, if you are pregnant or nursing a baby, seek the advice of a health care professional before using this product.

KEEP OUT OF REACH OF CHILDREN

Keep this and all medications out of the reach of children. In case of accidental overdose, seek professional assistance or contact a Poison Control Center immediately.

STORAGE AND HANDLING

Protect from light and heat.

Made in Germany

Distributed by:
SANUM USA Corp.
1465 Slater Road
Ferndale, WA 98248

Manufactured By:
Sanum-Kehlbeck
GmbH & Co. KG

Rev. 12/2007

PRINCIPAL DISPLAY PANEL - 100 mL Label

Pleo™ Chelate
HOMEOPATHIC
PREPARATION

Indications:
To optimize body minerals

3.38 fl oz
(100 mL)